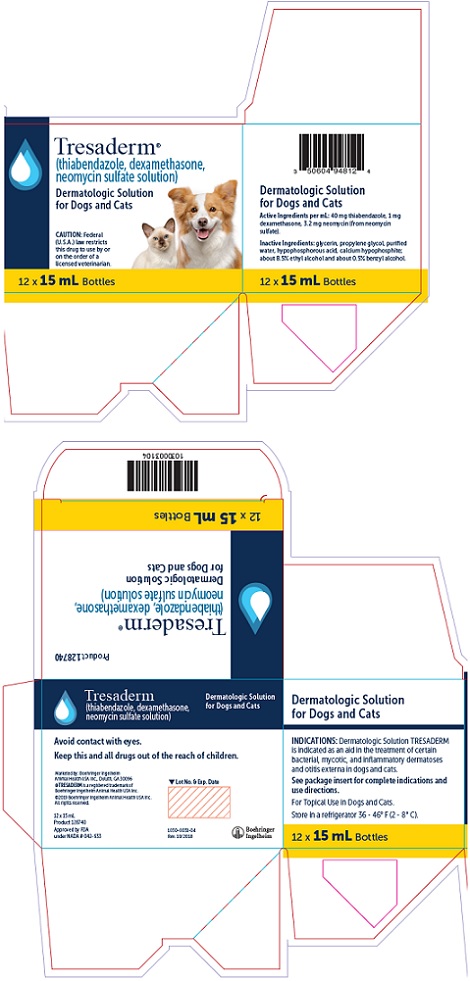 DRUG LABEL: TRESADERM
NDC: 0010-5587 | Form: SOLUTION
Manufacturer: Boehringer Ingelheim Animal Health USA Inc.
Category: animal | Type: PRESCRIPTION ANIMAL DRUG LABEL
Date: 20231117

ACTIVE INGREDIENTS: dexamethasone 1 mg/1 mL; neomycin sulfate 3.2 mg/1 mL; thiabendazole 40 mg/1 mL
INACTIVE INGREDIENTS: glycerin; propylene glycol; water; hypophosphorous acid; calcium hypophosphite; alcohol; benzyl alcohol

Tresaderm®
(thiabendazole, dexamethasone, neomycin sulfate solution)

Dermatologic Solution

Approved by FDA under NADA # 042-633

CAUTION

Federal (U.S.A.) law restricts this drug to use by or on the order of a licensed veterinarian.

DESCRIPTION

Dermatologic Solution TRESADERM® (thiabendazole, dexamethasone, neomycin sulfate solution) contains the following active ingredients per mL: 40 mg thiabendazole, 1 mg dexamethasone, 3.2 mg neomycin (from neomycin sulfate). Inactive ingredients: glycerin, propylene glycol, purified water, hypophosphorous acid, calcium hypophosphite; about 8.5% ethyl alcohol and about 0.5% benzyl alcohol.

INDICATIONS

Dermatologic Solution TRESADERM is indicated as an aid in the treatment of certain bacterial, mycotic, and inflammatory dermatoses and otitis externa in dogs and cats. Both acute and chronic forms of these skin disorders respond to treatment with TRESADERM. Many forms of dermatosis are caused by bacteria (chiefly Staphylococcus aureus, Proteus vulgaris and Pseudomonas aeruginosa). Moreover, these organisms often act as opportunistic or concurrent pathogens that may complicate already established mycotic skin disorders, or otoacariasis caused by Otodectes cynotis. The principal etiologic agents of dermatomycoses in dogs and cats are species of the genera Microsporum and Trichophyton. The efficacy of neomycin as an antibacterial agent, with activity against both gram-negative and gram-positive pathogens, is well documented. Detailed studies in various laboratories have verified the significant activity thiabendazole displays against the important dermatophytes. Dexamethasone, a synthetic adrenocorticoid steroid, inhibits the reaction of connective tissue to injury and suppresses the classic inflammatory manifestations of skin disease. The formulation for TRESADERM combines these several activities in a complementary form for control of the discomfort and direct treatment of dermatitis and otitis externa produced by the above-mentioned infectious agents.

DOSAGE AND ADMINISTRATION

Prior to the administration of Dermatologic Solution TRESADERM, remove the ceruminous, purulent or foreign materials from the ear canal, as well as the crust which may be associated with dermatoses affecting other parts of the body. The design of the container nozzle safely allows partial insertion into the ear canal for ease of administration. The amount to apply and the frequency of treatment are dependent upon the severity and extent of the lesions. Five to 15 drops should be instilled in the ear twice daily. In treating dermatoses affecting other than the ear the surface of the lesions should be well moistened (2 to 4 drops per square inch) with Dermatologic Solution TRESADERM twice daily. The volume required will be dependent upon the size of the lesion.

Application of TRESADERM should be limited to a period of not longer than one week.

PRECAUTIONS

On rare occasions dogs may be sensitive to neomycin. In these animals, application of the drug will result in erythema of the treated area, which may last 24 to 48 hours. Also, evidence of transient discomfort has been noted in some dogs when the drug was applied to fissured or denuded areas. The expression of pain may last 2 to 5 minutes. Application of Dermatologic Solution TRESADERM should be limited to periods not longer than one week.

While systemic side effects are not likely with topically applied corticosteroids, such a possibility should be considered if use of the solution is extensive and prolonged. If signs of salt and water retention or potassium excretion are noticed (increased thirst, weakness, lethargy, oliguria, gastrointestinal disturbances or tachycardia), treatment should be discontinued and appropriate measures taken to correct the electrolyte and fluid imbalance.

STORAGE AND HANDLING

Store in a refrigerator 36 - 46°F (2 - 8°C).

WARNING

For topical use in dogs and cats.
Avoid contact with eyes.

Keep this and all drugs out of the reach of children.

The Safety Data Sheet (SDS) contains more detailed occupational safety information. To report suspected adverse drug events, for technical assistance, or to obtain a copy of the Safety Data Sheet (SDS), contact Boehringer Ingelheim Animal Health USA Inc. at 1-888-637-4251. For additional information about adverse drug experience reporting for animal drugs, contact FDA at 1-888-FDA-VETS, or online at www.fda.gov/reportanimalae.

HOW SUPPLIED

Products 128740 & 128741 - Dermatologic Solution TRESADERM Veterinary is supplied in 7.5 mL and 15 mL dropper bottles, each in 12 bottle boxes.

Marketed by
Boehringer Ingelheim Animal Health USA Inc.
Duluth, Georgia 30096

© 2019 Boehringer Ingelheim Animal Health USA Inc. All rights reserved.

October 2018

®TRESADERM is a registered trademark of Boehringer Ingelheim Animal Health USA Inc.

PRINCIPAL DISPLAY PANEL - 15 mL Bottle Carton

Tresaderm®
(thiabendazole, dexamethasone, neomycin sulfate solution)

Dermatologic Solutionfor Dogs and Cats

CAUTION: Federal (U.S.A.) law restricts this drug to use by or on the order of a licensed veterinarian.

12 x 15 mL Bottles